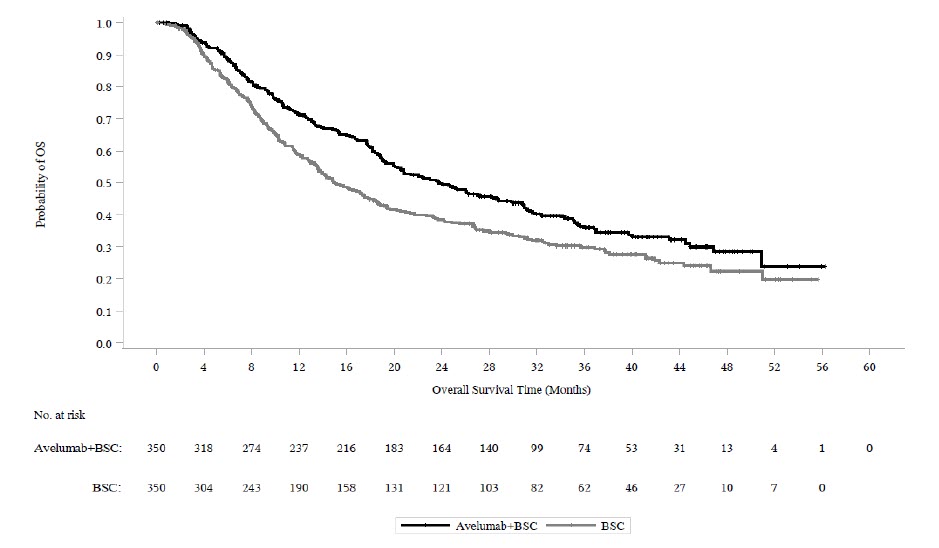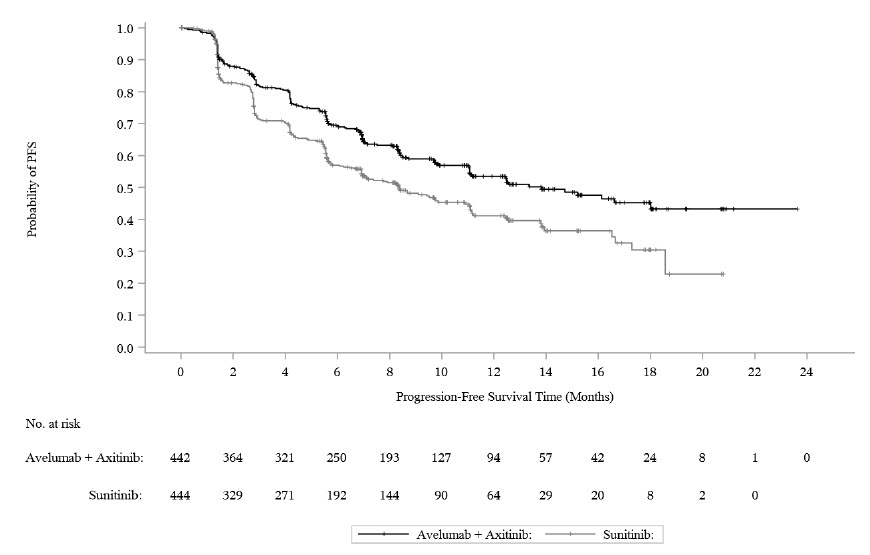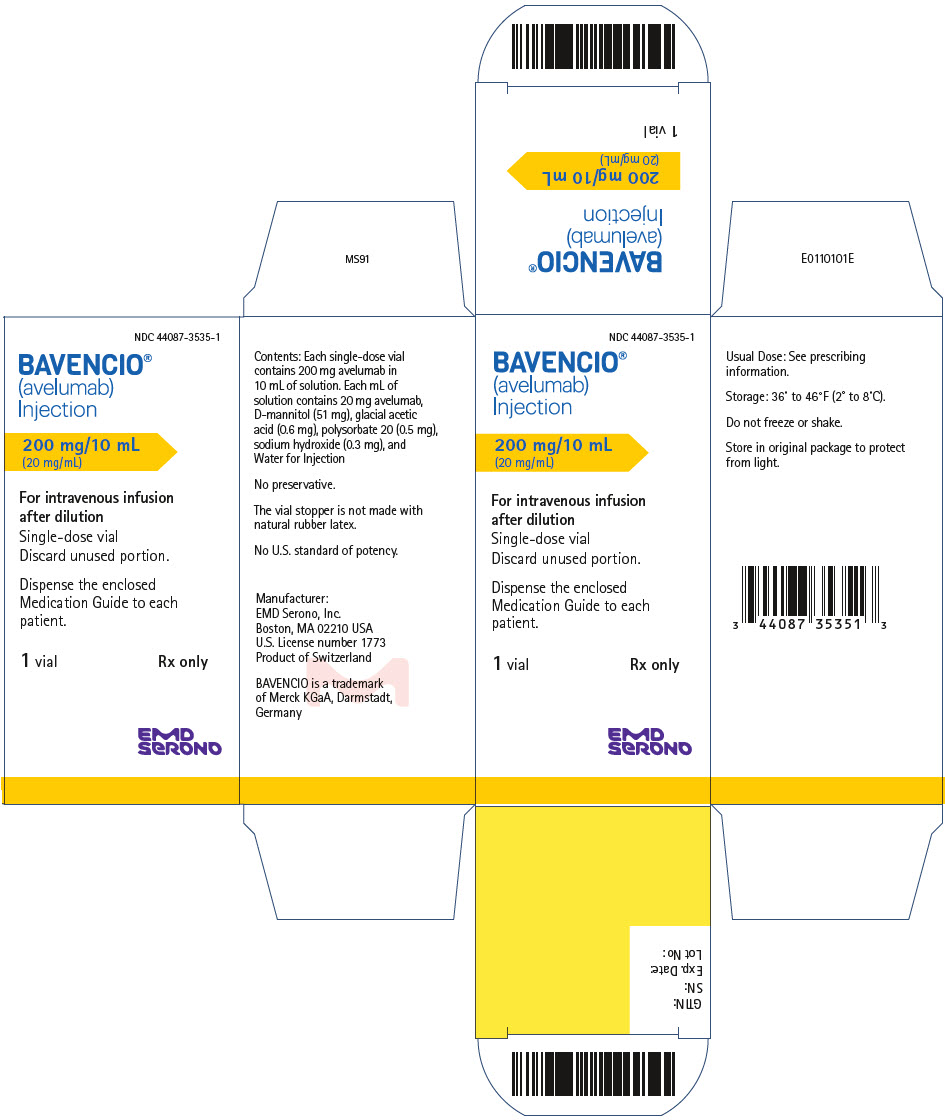 DRUG LABEL: BAVENCIO
NDC: 44087-3535 | Form: INJECTION, SOLUTION, CONCENTRATE
Manufacturer: EMD Serono, Inc.
Category: prescription | Type: HUMAN PRESCRIPTION DRUG LABEL
Date: 20250613

ACTIVE INGREDIENTS: avelumab 20 mg/1 mL
INACTIVE INGREDIENTS: MANNITOL; acetic acid; polysorbate 20; sodium hydroxide; water

HIGHLIGHTS OF PRESCRIBING INFORMATION

These highlights do not include all the information needed to use BAVENCIO safely and effectively. See full prescribing information for BAVENCIO.
BAVENCIO® (avelumab) injection, for intravenous use
Initial U.S. Approval: 2017

1 INDICATIONS AND USAGE

BAVENCIO is a programmed death ligand-1 (PD-L1) blocking antibody indicated for:

Merkel Cell Carcinoma (MCC)

- Adults and pediatric patients 12 years and older with metastatic MCC. (1.1, 14.1)

Urothelial Carcinoma (UC)

- Maintenance treatment of patients with locally advanced or metastatic UC that has not progressed with first-line platinum-containing chemotherapy. (1.2, 14.2)
- Patients with locally advanced or metastatic UC who:
  - Have disease progression during or following platinum-containing chemotherapy. (1.2, 14.2)
  - Have disease progression within 12 months of neoadjuvant or adjuvant treatment with platinum-containing chemotherapy. (1.2, 14.2)

Renal Cell Carcinoma (RCC)

- First-line treatment, in combination with axitinib, of patients with advanced RCC. (1.3, 14.3)

2 DOSAGE AND ADMINISTRATION

- Premedicate for the first 4 infusions and subsequently as needed. (2.1)
- Merkel Cell Carcinoma: 800 mg every 2 weeks. (2.2)
- Urothelial Carcinoma; 800 mg every 2 weeks. (2.3)
- Renal Cell Carcinoma: 800 mg every 2 weeks in combination with axitinib 5 mg orally twice daily. (2.4)

Administer BAVENCIO as an intravenous infusion over 60 minutes.

3 DOSAGE FORMS AND STRENGTHS

Injection: 200 mg/10 mL (20 mg/mL) solution in single-dose vial. (3)

4 CONTRAINDICATIONS

None. (4)

5 WARNINGS AND PRECAUTIONS

- Immune-Mediated Adverse Reactions (5.1)
  - Immune-mediated adverse reactions, which may be severe or fatal, can occur in any organ system or tissue, including the following: immune-mediated pneumonitis, immune-mediated colitis, immune-mediated hepatitis, immune-mediated endocrinopathies, immune-mediated nephritis with renal dysfunction, immune-mediated dermatologic adverse reactions, and may result in solid organ transplant rejection.
  - Monitor for early identification and management. Evaluate liver enzymes, creatinine, and thyroid function at baseline and periodically during treatment.
  - Withhold or permanently discontinue based on severity and type of reaction.
- Infusion-related reactions: Interrupt, slow the rate of infusion, or permanently discontinue BAVENCIO based on severity of reaction. (5.2)
- Complications of allogeneic HSCT: Fatal and other serious complications can occur in patients who receive allogeneic HSCT before or after being treated with a PD-1/PD-L1 blocking antibody. (5.3)
- Major adverse cardiovascular events: Optimize management of cardiovascular risk factors. Discontinue BAVENCIO in combination with axitinib for Grade 3-4 events. (5.4)
- Embryo-fetal toxicity: BAVENCIO can cause fetal harm. Advise females of reproductive potential of the potential risk to a fetus and use of effective contraception. (5.5, 8.1, 8.3)

6 ADVERSE REACTIONS

Most common adverse reactions (≥ 20%) in patients were:

- MCC:
  - Fatigue, musculoskeletal pain, infusion-related reaction, rash, nausea, constipation, cough, and diarrhea. (6.1)
- UC:
  - Maintenance treatment: fatigue, musculoskeletal pain, urinary tract infection, and rash. (6.1)
  - Previously-treated: fatigue, infusion-related reaction, musculoskeletal pain, nausea, decreased appetite, and urinary tract infection. (6.1)
- RCC (with axitinib): diarrhea, fatigue, hypertension, musculoskeletal pain, nausea, mucositis, palmar-plantar erythrodysesthesia, dysphonia, decreased appetite, hypothyroidism, rash, hepatotoxicity, cough, dyspnea, abdominal pain, and headache. (6.1)

To report SUSPECTED ADVERSE REACTIONS, contact EMD Serono at 1-800-283-8088 ext. 5563 or FDA at 1-800-FDA-1088 or www.fda.gov/medwatch.

8 USE IN SPECIFIC POPULATIONS

Lactation: Advise not to breastfeed. (8.2)

FULL PRESCRIBING INFORMATION

1 INDICATIONS AND USAGE

1.1 Metastatic Merkel Cell Carcinoma

BAVENCIO (avelumab) is indicated for the treatment of adults and pediatric patients 12 years and older with metastatic Merkel cell carcinoma (MCC) [see Clinical Studies (14.1)].

1.2 Locally Advanced or Metastatic Urothelial Carcinoma

First-Line Maintenance Treatment of Urothelial Carcinoma

BAVENCIO is indicated for the maintenance treatment of patients with locally advanced or metastatic urothelial carcinoma (UC) that has not progressed with first-line platinum-containing chemotherapy [see Clinical Studies (14.2)].

Previously-treated Urothelial Carcinoma

BAVENCIO is indicated for the treatment of patients with locally advanced or metastatic urothelial carcinoma (UC) who:

- Have disease progression during or following platinum-containing chemotherapy
- Have disease progression within 12 months of neoadjuvant or adjuvant treatment with platinum-containing chemotherapy [see Clinical Studies (14.2)].

1.3 Advanced Renal Cell Carcinoma

BAVENCIO in combination with axitinib is indicated for the first-line treatment of patients with advanced renal cell carcinoma (RCC) [see Clinical Studies (14.3)].

2 DOSAGE AND ADMINISTRATION

2.1 Premedication

Premedicate patients with an antihistamine and with acetaminophen prior to the first 4 infusions of BAVENCIO. Premedication should be administered for subsequent BAVENCIO doses based upon clinical judgment and presence/severity of prior infusion reactions [see Dosage and Administration (2.5) and Warnings and Precautions (5.2)].

2.2 Recommended Dosage for MCC

The recommended dosage of BAVENCIO is 800 mg administered as an intravenous infusion over 60 minutes every 2 weeks until disease progression or unacceptable toxicity.

2.3 Recommended Dosage for UC

The recommended dosage of BAVENCIO is 800 mg administered as an intravenous infusion over 60 minutes every 2 weeks until disease progression or unacceptable toxicity.

2.4 Recommended Dosage for RCC

The recommended dosage of BAVENCIO is 800 mg administered as an intravenous infusion over 60 minutes every 2 weeks in combination with axitinib 5 mg orally taken twice daily (12 hours apart) with or without food until disease progression or unacceptable toxicity.

When axitinib is used in combination with BAVENCIO, dose escalation of axitinib above the initial 5 mg dose may be considered at intervals of two weeks or longer. Review the Full Prescribing Information for axitinib prior to initiation.

2.5 Dose Modifications

No dose reduction for BAVENCIO is recommended. In general, withhold BAVENCIO for severe (Grade 3) immune-mediated adverse reactions. Permanently discontinue BAVENCIO for life-threatening (Grade 4) immune-mediated adverse reactions, recurrent severe (Grade 3) immune-mediated reactions that require systemic immunosuppressive treatment, or an inability to reduce corticosteroid dose to 10 mg or less of prednisone or equivalent per day within 12 weeks of initiating corticosteroids.

Dosage modifications for BAVENCIO for adverse reactions that require management different from these general guidelines are summarized in Table 1.

Table 1: Recommended Monotherapy Dosage Modifications for Adverse Reactions
Adverse Reaction | Severity [Based on Common Terminology Criteria for Adverse Events (CTCAE), version 4.03] | Dosage Modification
Immune-Mediated Adverse Reactions [see Warnings and Precautions (5.1)]
Pneumonitis | Grade 2 | Withhold [Resume in patients with complete or partial resolution (Grade 0 to 1) after corticosteroid taper. Permanently discontinue if no complete or partial resolution within 12 weeks of last dose or inability to reduce prednisone to 10 mg per day or less (or equivalent) within 12 weeks of initiating corticosteroids.]
Pneumonitis | Grade 3 or 4 | Permanently discontinue
Colitis | Grade 2 or 3 | Withhold
Colitis | Grade 4 | Permanently discontinue
Hepatitis with no tumor involvement of the liver For liver enzyme elevations in patients treated with combination therapy, see Table 2 | AST or ALT increases to more than 3 and up to 8 times ULN or Total bilirubin increases to more than 1.5 and up to 3 times ULN | Withhold
Hepatitis with no tumor involvement of the liver For liver enzyme elevations in patients treated with combination therapy, see Table 2 | AST or ALT increases to more than 8 times ULN or Total bilirubin increases to more than 3 times ULN | Permanently discontinue
Hepatitis with tumor involvement of the liver [If AST and ALT are less than or equal to ULN at baseline, withhold or permanently discontinue BAVENCIO based on recommendations for hepatitis where there is no tumor involvement of the liver.] | Baseline AST or ALT is more than 1 and up to 3 times ULN and increases to more than 5 and up to 10 times ULN or Baseline AST or ALT is more than 3 and up to 5 times ULN and increases to more than 8 and up to 10 times ULN | Withhold
Hepatitis with tumor involvement of the liver [If AST and ALT are less than or equal to ULN at baseline, withhold or permanently discontinue BAVENCIO based on recommendations for hepatitis where there is no tumor involvement of the liver.] | AST or ALT increases to more than 10 times ULN or Total bilirubin increases to more than 3 times ULN | Permanently discontinue
Endocrinopathies | Grade 3 or 4 | Withhold until clinically stable or permanently discontinue depending on severity
Nephritis with Renal Dysfunction | Grade 2 or 3 increased blood creatinine | Withhold
Nephritis with Renal Dysfunction | Grade 4 increased blood creatinine | Permanently discontinue
Exfoliative Dermatologic Conditions | Suspected SJS, TEN, or DRESS | Withhold
Exfoliative Dermatologic Conditions | Confirmed SJS, TEN, or DRESS | Permanently discontinue
Myocarditis | Grade 2, 3 or 4 | Permanently discontinue
Neurological Toxicities | Grade 2 | Withhold
Neurological Toxicities | Grade 3 or 4 | Permanently discontinue
Other Adverse Reactions
Infusion-related reactions [see Warnings and Precautions (5.2)] | Grade 1 or 2 | Interrupt or slow the rate of infusion
Infusion-related reactions [see Warnings and Precautions (5.2)] | Grade 3 or 4 | Permanently discontinue
ALT = alanine aminotransferase, AST = aspartate aminotransferase, ULN = upper limit normal, SJS = Stevens-Johnson syndrome, TEN = toxic epidermal necrosis, DRESS = drug rash with eosinophilia and systemic symptoms

Table 2 presents dosage modifications that are different from those described above in Table 1 for BAVENCIO used as monotherapy or in the Full Prescribing Information for the drug administered in combination.

Table 2: Recommended Specific Dosage Modifications for Adverse Reactions for Combination Therapy [see Warnings and Precautions (5.1)]
Treatment | Adverse Reaction | Severity [Based on Common Terminology Criteria for Adverse Events (CTCAE), version 4.03] | Dosage Modification
BAVENCIO in combination with axitinib | Liver enzyme elevations | ALT or AST at least 3 times ULN but less than 10 times ULN without concurrent total bilirubin at least 2 times ULN | Withhold both BAVENCIO and axitinib until adverse reactions recover to Grades 0-1 [Consider corticosteroid therapy] Consider rechallenge with BAVENCIO or axitinib or sequential rechallenge with both BAVENCIO and axitinib after recovery [Dose reduction according to the axitinib Full Prescribing Information should be considered if rechallenging with axitinib.]
BAVENCIO in combination with axitinib | Liver enzyme elevations | ALT or AST at least 10 times ULN or more than 3 times ULN with concurrent total bilirubin at least 2 times ULN | Permanently discontinue both BAVENCIO and axitinib

2.6 Preparation and Administration

Preparation

- Visually inspect vial for particulate matter and discoloration. BAVENCIO is a clear, colorless to slightly yellow solution. Discard vial if the solution is cloudy, discolored, or contains particulate matter.
- Withdraw the required volume of BAVENCIO from the vial(s) and inject it into a 250 mL infusion bag containing either 0.9% Sodium Chloride Injection or 0.45% Sodium Chloride Injection.
- Gently invert the bag to mix the diluted solution and avoid foaming or excessive shearing.
- Inspect the solution to ensure it is clear, colorless, and free of visible particles.
- Discard any partially used or empty vials.

Storage of diluted BAVENCIO solution

Protect from light.

Store diluted BAVENCIO solution:

- At room temperature up to 77°F (25°C) for no more than 4 hours from the time of dilution.

Or

- Under refrigeration at 36°F to 46°F (2°C to 8°C) for no more than 24 hours from the time of dilution. If refrigerated, allow the diluted solution to come to room temperature prior to administration.

Do not freeze or shake diluted solution.

Administration

- Administer the diluted solution over 60 minutes through an intravenous line containing a sterile, non-pyrogenic, low protein binding in-line filter (pore size of 0.2 micron).
- Do not co-administer other drugs through the same intravenous line.

3 DOSAGE FORMS AND STRENGTHS

Injection: 200 mg/10 mL (20 mg/mL), clear, colorless to slightly yellow solution in a single-dose vial.

4 CONTRAINDICATIONS

None.

5 WARNINGS AND PRECAUTIONS

5.1 Severe and Fatal Immune-Mediated Adverse Reactions

BAVENCIO is a monoclonal antibody that belongs to a class of drugs that bind to either the programmed death-receptor 1 (PD-1) or the PD-ligand 1 (PD-L1), blocking the PD-1/PD-L1 pathway, thereby removing inhibition of the immune response, potentially breaking peripheral tolerance and inducing immune-mediated adverse reactions. Important immune-mediated adverse reactions listed under Warnings and Precautions may not include all possible severe and fatal immune-mediated reactions.

Immune-mediated adverse reactions, which may be severe or fatal, can occur in any organ system or tissue. Immune-mediated adverse reactions can occur at any time after starting treatment with a PD-1/PD-L1 blocking antibody. While immune-mediated adverse reactions usually manifest during treatment with PD-1/PD-L1 blocking antibodies, immune-mediated adverse reactions can also manifest after discontinuation of PD-1/PD-L1 blocking antibodies.

Early identification and management of immune-mediated adverse reactions are essential to ensure safe use of PD-1/PD-L1 blocking antibodies. Monitor patients closely for symptoms and signs that may be clinical manifestations of underlying immune-mediated adverse reactions. Evaluate liver enzymes, creatinine, and thyroid function at baseline and periodically during treatment. In cases of suspected immune-mediated adverse reactions, initiate appropriate workup to exclude alternative etiologies, including infection. Institute medical management promptly, including specialty consultation as appropriate.

Withhold or permanently discontinue BAVENCIO depending on severity [see Dosage and Administration (2.5)]. In general, if BAVENCIO requires interruption or discontinuation, administer systemic corticosteroid therapy (1 to 2 mg/kg/day prednisone or equivalent) until improvement to Grade 1 or less. Upon improvement to Grade 1 or less, initiate corticosteroid taper and continue to taper over at least 1 month. Consider administration of other systemic immunosuppressants in patients whose immune-mediated adverse reactions are not controlled with corticosteroid therapy.

Toxicity management guidelines for adverse reactions that do not necessarily require systemic corticosteroids (e.g., endocrinopathies and dermatologic reactions) are discussed below.

Immune-Mediated Pneumonitis

BAVENCIO can cause immune-mediated pneumonitis. Immune-mediated pneumonitis occurred in 1.1% (21/1854) of patients receiving BAVENCIO, including fatal (0.1%), Grade 4 (0.1%), Grade 3 (0.3%) and Grade 2 (0.6%) adverse reactions. Pneumonitis led to permanent discontinuation of BAVENCIO in 0.3% and withholding of BAVENCIO in 0.3% of patients.

Systemic corticosteroids were required in all (21/21) patients with pneumonitis. Pneumonitis resolved in 57% (12/21) of the patients. Of the 5 patients in whom BAVENCIO was withheld for pneumonitis, 5 reinitiated treatment with BAVENCIO after symptom improvement; of these, none had recurrence of pneumonitis.

With other PD-1/PD-L1 blocking antibodies, the incidence of pneumonitis is higher in patients who have received prior thoracic radiation.

Immune-Mediated Colitis

BAVENCIO can cause immune-mediated colitis. The primary component of the immune-mediated colitis consisted of diarrhea. Cytomegalovirus (CMV) infection/reactivation has been reported in patients with corticosteroid-refractory immune-mediated colitis. In cases of corticosteroid-refractory colitis, consider repeating infectious workup to exclude alternative etiologies.

Immune-mediated colitis occurred in 1.5% (27/1854) of patients receiving BAVENCIO, including Grade 3 (0.4%) and Grade 2 (0.8%) adverse reactions. Colitis led to permanent discontinuation of BAVENCIO in 0.5% and withholding of BAVENCIO in 0.4% of patients.

Systemic corticosteroids were required in all (27/27) patients with colitis. Colitis resolved in 70% (19/27) of the patients. Of the 8 patients in whom BAVENCIO was withheld for colitis, 5 reinitiated treatment with BAVENCIO after symptom improvement; of these, 40% had recurrence of colitis.

Hepatotoxicity and Immune-Mediated Hepatitis

BAVENCIO as a single agent

BAVENCIO can cause immune-mediated hepatitis. Immune-mediated hepatitis occurred in 1.1% (20/1854) of patients receiving BAVENCIO, including fatal (0.1%), Grade 3 (0.8%), and Grade 2 (0.2%) adverse reactions. Hepatitis led to permanent discontinuation of BAVENCIO in 0.6% and withholding of BAVENCIO in 0.2% of patients.

Systemic corticosteroids were required in all (20/20) patients with hepatitis. Hepatitis resolved in 60% (12/20) of the patients. Of the 4 patients in whom BAVENCIO was withheld for hepatitis, 4 reinitiated treatment with BAVENCIO after symptom improvement; of these, 25% had recurrence of hepatitis.

BAVENCIO with Axitinib

BAVENCIO in combination with axitinib can cause hepatotoxicity with higher-than-expected frequencies of Grade 3 and 4 ALT and AST elevation compared to BAVENCIO alone. Consider more frequent monitoring of liver enzymes as compared to when the drugs are used as monotherapy. For elevated liver enzymes, interrupt BAVENCIO and axitinib and consider administering corticosteroids as needed [see Dosage and Administration (2.5)].

In patients treated with BAVENCIO in combination with axitinib in the advanced RCC trials, increased ALT and increased AST were reported in 9% (Grade 3) and 7% (Grade 4) of patients. In patients with ALT ≥ 3 times ULN (Grades 2-4, n=82), ALT resolved to Grades 0-1 in 92%. Among the 73 patients who were rechallenged with either BAVENCIO (n=3) or axitinib (n=25) administered as a single agent or with both (n=45), recurrence of ALT ≥3 times ULN was observed in no patient receiving BAVENCIO, 6 patients receiving axitinib, and 15 patients receiving both BAVENCIO and axitinib. Twenty-two (88%) patients with a recurrence of ALT ≥3 ULN subsequently recovered to Grade 0-1 from the event. Immune-mediated hepatitis was reported in 7% of patients, including 4.9% with Grade 3 or 4 immune-mediated hepatitis. Hepatotoxicity led to permanent discontinuation in 6.5% and immune-mediated hepatitis led to permanent discontinuation of either BAVENCIO or axitinib in 5.3% of patients. Thirty-four patients were treated with corticosteroids and one patient was treated with a non-steroidal immunosuppressant. Resolution of hepatitis occurred in 31 of the 35 patients at the time of data cut-off.

Immune-Mediated Endocrinopathies

Adrenal Insufficiency

BAVENCIO can cause primary or secondary adrenal insufficiency. For Grade 2 or higher adrenal insufficiency, initiate symptomatic treatment, including hormone replacement, as clinically indicated. Withhold BAVENCIO depending on severity [see Dosage and Administration (2.5)].

Immune-mediated adrenal insufficiency occurred in 0.6% (11/1854) of patients receiving BAVENCIO, including Grade 3 (0.1%), and Grade 2 (0.4%) adverse reactions. Adrenal insufficiency led to permanent discontinuation of BAVENCIO in 0.1% and withholding of BAVENCIO in 0.1% of patients.

Systemic corticosteroids were required in all (11/11) patients with adrenal insufficiency. Adrenal insufficiency resolved in 18% (2/11) of patients. Of the 2 patients in whom BAVENCIO was withheld for adrenal insufficiency, none reinitiated treatment with BAVENCIO.

Hypophysitis

BAVENCIO can cause immune-mediated hypophysitis. Hypophysitis can present with acute symptoms associated with mass effect such as headache, photophobia, or visual field defects. Hypophysitis can cause hypopituitarism. Initiate hormone replacement, as clinically indicated. Withhold or permanently discontinue BAVENCIO depending on severity [see Dosage and Administration (2.5)].

Immune-mediated pituitary disorders occurred in 0.1% (1/1854) of patients receiving BAVENCIO which was a Grade 2 (0.1%) adverse reactions. Hypopituitarism did not lead to withholding of BAVENCIO in this patient. Systemic corticosteroids were not required in this patient.

Thyroid Disorders

BAVENCIO can cause immune-mediated thyroid disorders. Thyroiditis can present with or without endocrinopathy. Hypothyroidism can follow hyperthyroidism. Initiate hormone replacement for hypothyroidism or institute medical management of hyperthyroidism, as clinically indicated. Withhold or permanently discontinue BAVENCIO depending on severity [see Dosage and Administration (2.5)].

Thyroiditis occurred in 0.2% (4/1854) of patients receiving BAVENCIO, including Grade 2 (0.1%) adverse reactions. Thyroiditis did not lead to permanent discontinuation or withholding of BAVENCIO in any patients. No patients with thyroiditis required systemic corticosteroids. Thyroiditis did not resolve in any patients (0/4).

Hyperthyroidism occurred in 0.4% (8/1854) of patients receiving BAVENCIO, including Grade 2 (0.3%) adverse reactions. Hyperthyroidism did not lead to permanent discontinuation of BAVENCIO in any patients and led to withholding of BAVENCIO in 0.1% of patients. Systemic corticosteroids were required in 25% (2/8) of patients with hyperthyroidism. Hyperthyroidism resolved in 88% (7/8) of the patients. Of the 2 patients in whom BAVENCIO was withheld for hyperthyroidism, 2 reinitiated treatment with BAVENCIO after symptom improvement; of these, none had recurrence of hyperthyroidism.

Hypothyroidism occurred in 5% (97/1854) of patients receiving BAVENCIO, including Grade 3 (0.2%) and Grade 2 (3.6%) adverse reactions. Hypothyroidism led to permanent discontinuation of BAVENCIO in 0.1% and withholding of BAVENCIO in 0.4% of patients. Systemic corticosteroids were required in 6% (6/97) of patients with hypothyroidism. Hypothyroidism resolved in 6% (6/97) of the patients. Of the 8 patients in whom BAVENCIO was withheld for hypothyroidism, none reinitiated BAVENCIO.

Type I Diabetes Mellitus, which can present with Diabetic Ketoacidosis: Monitor patients for hyperglycemia or other signs and symptoms of diabetes. Initiate treatment with insulin as clinically indicated. Withhold BAVENCIO depending on severity [see Dosage and Administration (2.5)].

Immune-mediated Type I diabetes mellitus occurred in 0.2% (3/1854) of patients receiving BAVENCIO, including Grade 3 (0.2%) adverse reactions. Type I diabetes mellitus led to permanent discontinuation of BAVENCIO in 0.1% of patients. Type I diabetes mellitus did not lead to withholding of BAVENCIO in any patient. Systemic corticosteroids were not required in any patient with Type I diabetes mellitus. Type I diabetes mellitus resolved in no patient and all patients required ongoing insulin treatment.

Immune-Mediated Nephritis with Renal Dysfunction

BAVENCIO can cause immune-mediated nephritis.

Immune-mediated nephritis with renal dysfunction occurred in 0.1% (2/1854) of patients receiving BAVENCIO, including Grade 3 (0.1%) and Grade 2 (0.1%) adverse reactions. Nephritis with renal dysfunction led to permanent discontinuation of BAVENCIO in 0.1% of patients. Nephritis did not lead to withholding of BAVENCIO in any patient.

Systemic corticosteroids were required in 100% of patients with nephritis with renal dysfunction. Nephritis with renal dysfunction resolved in 50% of the patients.

Immune-Mediated Dermatologic Adverse Reactions

BAVENCIO can cause immune-mediated rash or dermatitis. Exfoliative dermatitis, including Stevens Johnson Syndrome, DRESS, and toxic epidermal necrolysis (TEN), has occurred with PD-1/PD-L1 blocking antibodies. Topical emollients and/or topical corticosteroids may be adequate to treat mild to moderate non-exfoliative rashes. Withhold or permanently discontinue BAVENCIO depending on severity [see Dosage and Administration (2.5)].

Immune-mediated dermatologic adverse reactions occurred in 6% (108/1854) of patients receiving BAVENCIO, including Grade 3 (0.1%) and Grade 2 (1.9%) adverse reactions. Dermatologic adverse reactions led to permanent discontinuation of BAVENCIO in 0.3% of patients and withholding of BAVENCIO in 0.4% of patients.

Systemic corticosteroids were required in 25% (27/108) of patients with dermatologic adverse reactions. One patient required the addition of tacrolimus to high-dose corticosteroids.

Dermatologic adverse reactions resolved in 46% (50/108) of the patients. Of the 8 patients in whom BAVENCIO was withheld for dermatologic adverse reactions, 4 reinitiated treatment with BAVENCIO after symptom improvement; of these, none had recurrence of dermatologic adverse reaction.

Other Immune-Mediated Adverse Reactions

The following clinically significant immune-mediated adverse reactions occurred at an incidence of < 1% (unless otherwise noted) in patients who received BAVENCIO or were reported with the use of other PD-1/PD-L1 blocking antibodies. Severe or fatal cases have been reported for some of these adverse reactions.

Cardiac/Vascular: Myocarditis, pericarditis, vasculitis.

Gastrointestinal: Pancreatitis to include increases in serum amylase and lipase levels, gastritis, duodenitis.

Nervous System: Meningitis, encephalitis, myelitis and demyelination, myasthenic syndrome/myasthenia gravis (including exacerbation), Guillain-Barré syndrome, nerve paresis, autoimmune neuropathy.

Ocular: Uveitis, iritis, and other ocular inflammatory toxicities can occur. Some cases can be associated with retinal detachment. Various grades of visual impairment, including blindness, can occur. If uveitis occurs in combination with other immune-mediated adverse reactions, consider a Vogt-Koyanagi-Harada like syndrome, as this may require treatment with systemic corticosteroids to reduce the risk of permanent vision loss.

Musculoskeletal and Connective Tissue: Myositis/polymyositis, rhabdomyolysis (and associated sequelae including renal failure), arthritis, polymyalgia rheumatica.

Endocrine: Hypoparathyroidism.

Other (Hematologic/Immune): Hemolytic anemia, aplastic anemia, hemophagocytic lymphohistiocytosis, systemic inflammatory response syndrome, histiocytic necrotizing lymphadenitis (Kikuchi lymphadenitis), sarcoidosis, immune thrombocytopenic purpura, solid organ transplant rejection, other transplant (including corneal graft) rejection.

5.2 Infusion-Related Reactions

BAVENCIO can cause severe or life-threatening infusion-related reactions [see Adverse Reactions (6.1)]. Premedicate with antihistamine and acetaminophen prior to the first 4 infusions. Monitor patients for signs and symptoms of infusion-related reactions including pyrexia, chills, flushing, hypotension, dyspnea, wheezing, back pain, abdominal pain, and urticaria. Interrupt or slow the rate of infusion for mild or moderate infusion-related reactions. Stop the infusion and permanently discontinue BAVENCIO for severe (Grade 3) or life-threatening (Grade 4) infusion-related reactions [see Dosage and Administration (2.5) and Adverse Reactions (6.1)].

Infusion-related reactions occurred in 26% of patients treated with BAVENCIO including 3 (0.2%) Grade 4 and 10 (0.5%) Grade 3 infusion-related reactions. Ninety-three percent of patients received premedication with antihistamine and acetaminophen. Eleven (85%) of the 13 patients with Grade ≥ 3 reactions were treated with intravenous corticosteroids. Fifteen percent of patients had infusion-related reactions that occurred after the BAVENCIO infusion was completed.

5.3 Complications of Allogeneic HSCT

Fatal and other serious complications can occur in patients who receive allogeneic hematopoietic stem cell transplantation (HSCT) before or after being treated with a PD-1/PD-L1 blocking antibody. Transplant-related complications include hyperacute graft-versus-host-disease (GVHD), acute GVHD, chronic GVHD, hepatic veno-occlusive disease (VOD) after reduced intensity conditioning, and steroid-requiring febrile syndrome (without an identified infectious cause). These complications may occur despite intervening therapy between PD-1/PD-L1 blockade and allogeneic HSCT.

Follow patients closely for evidence of transplant-related complications and intervene promptly. Consider the benefit versus risks of treatment with a PD-1/PD-L1 blocking antibody prior to or after an allogeneic HSCT.

5.4 Major Adverse Cardiovascular Events (MACE)

BAVENCIO in combination with axitinib can cause severe and fatal cardiovascular events. Consider baseline and periodic evaluations of left ventricular ejection fraction. Monitor for signs and symptoms of cardiovascular events. Optimize management of cardiovascular risk factors, such as hypertension, diabetes, or dyslipidemia. Discontinue BAVENCIO and axitinib for Grade 3-4 cardiovascular events.

MACE occurred in 7% of patients with advanced RCC treated with BAVENCIO in combination with axitinib compared to 3.4% treated with sunitinib in a randomized trial, JAVELIN Renal 101. These events included death due to cardiac events (1.4%), Grade 3-4 myocardial infarction (2.8%), and Grade 3-4 congestive heart failure (1.8%). Median time to onset of MACE was 4.2 months (range: 2 days to 24.5 months).

5.5 Embryo-Fetal Toxicity

Based on its mechanism of action, BAVENCIO can cause fetal harm when administered to a pregnant woman. Animal studies have demonstrated that inhibition of the PD-1/PD-L1 pathway can lead to increased risk of immune-mediated rejection of the developing fetus resulting in fetal death. If this drug is used during pregnancy, or if the patient becomes pregnant while taking BAVENCIO, inform the patient of the potential risk to a fetus. Advise females of childbearing potential to use effective contraception during treatment with BAVENCIO and for at least one month after the last dose of BAVENCIO [see Use in Specific Populations (8.1, 8.3)].

6 ADVERSE REACTIONS

The following clinically significant adverse reactions are described elsewhere in the labeling:

- Severe and fatal immune-mediated adverse reactions [see Warnings and Precautions (5.1)]
- Infusion-related reactions [see Warnings and Precautions (5.2)]
- Complications of allogeneic HSCT [see Warnings and Precautions (5.3)]
- Major adverse cardiovascular events [see Warnings and Precautions (5.4)]

6.1 Clinical Trials Experience

Because clinical trials are conducted under widely varying conditions, adverse reaction rates observed in the clinical trials of a drug cannot be directly compared to rates in the clinical trials of another drug and may not reflect the rates observed in practice.

The data described in the WARNINGS AND PRECAUTIONS section reflect exposure to BAVENCIO 10 mg/kg intravenously every 2 weeks as a single agent in 1854 patients enrolled in the JAVELIN Merkel 200 and JAVELIN Solid Tumor trials and to BAVENCIO 10 mg/kg intravenously every 2 weeks in combination with axitinib 5 mg orally twice daily in 489 patients enrolled in the JAVELIN Renal 100 and JAVELIN Renal 101 trials. In the BAVENCIO monotherapy population, 25% of patients were exposed for ≥ 6 months and 9% were exposed for ≥ 12 months. The population characteristics of BAVENCIO in combination with axitinib are shown below. When BAVENCIO was used in combination with axitinib, 70% of patients were exposed for ≥ 6 months and 31% were exposed for ≥ 12 months. The following criteria were used to classify an adverse reaction as immune-mediated: onset within 90 days after last dose of BAVENCIO, no spontaneous resolution within 7 days of onset, treatment with corticosteroids or other immunosuppressant or hormone replacement therapy, biopsy consistent with immune-mediated reaction, and no other clear etiology.

Metastatic Merkel Cell Carcinoma

The safety of BAVENCIO was evaluated in 204 patients enrolled in the JAVELIN Merkel 200 trial with metastatic MCC. Patients received BAVENCIO 10 mg/kg intravenously every 2 weeks or 800 mg intravenously every 2 weeks until disease progression or unacceptable toxicity.

The median duration of exposure to BAVENCIO was 4.1 months (range: 2 weeks to 48 months). [see Clinical Studies (14.1)].

Serious adverse reactions occurred in 52% of patients receiving BAVENCIO. The most frequent serious adverse reactions (≥ 2% of patients) were general physical health deterioration, anemia, abdominal pain, acute kidney injury, sepsis, hyponatremia, and infusion-related reaction.

Permanent discontinuation of BAVENCIO due to an adverse reaction occurred in 27% of patients. The most frequent adverse reactions (> 1% of patients) that resulted in permanent discontinuation were infusion-related reaction, anemia, increased ALT, and increased AST.

Dosage interruptions of BAVENCIO due to an adverse reaction, excluding temporary interruptions due to infusion-related reactions, occurred in 29% of patients. The most frequent adverse reactions (> 1% of patients) that required dosage interruption were nasopharyngitis, anemia, diarrhea, lung infection, and ALT increased.

The most common adverse reactions (≥ 20%) that occurred in patients receiving BAVENCIO were fatigue, musculoskeletal pain, infusion-related reaction, rash, nausea, constipation, cough, and diarrhea.

Table 3 and Table 4 summarize the adverse reactions and laboratory abnormalities, respectively, that occurred in patients receiving BAVENCIO.

Table 3: Adverse Reactions in ≥ 10% of Patients with Metastatic MCC Receiving BAVENCIO in the JAVELIN Merkel 200 Trial
Adverse Reactions | BAVENCIO (N=204)
Adverse Reactions | All Grades % | Grade 3-4 %
General Disorders
Fatigue [Includes fatigue and asthenia.] | 47 | 2.9
Infusion-related reaction [Includes infusion-related reaction, chills, pyrexia, back pain, hypotension, drug hypersensitivity, dyspnea, flushing and hypersensitivity.] | 26 | 0.5
Edema [Includes peripheral edema, peripheral swelling, and genital edema.] | 17 | 0
Musculoskeletal and Connective Tissue Disorders
Musculoskeletal pain [Includes musculoskeletal pain, back pain, pain in extremity, myalgia, musculoskeletal pain, and neck pain.] | 29 | 1.5
Arthralgia | 13 | 0.5
Skin and Subcutaneous Tissue Disorders
Rash [Includes rash, erythema, rash maculo-papular, rash pruritic, dermatitis bullous, rash erythematous, and rash macular.] | 25 | 0
Pruritus [Includes pruritus and pruritus generalized.] | 16 | 0.5
Gastrointestinal Disorders
Nausea | 23 | 0
Constipation | 22 | 0.5
Diarrhea [Includes diarrhea and colitis.] | 21 | 1
Abdominal pain [Includes abdominal pain, abdominal pain upper, and abdominal pain lower.] | 16 | 3.4
Vomiting | 12 | 1
Respiratory, Thoracic and Mediastinal Disorders
Cough | 22 | 0
Dyspnea [Includes dyspnea and dyspnea exertional.] | 15 | 1
Metabolism and Nutrition Disorders
Decreased appetite | 18 | 3.4
Decreased weight | 16 | 0.5
Vascular Disorders
Hypertension | 11 | 6

Other clinically significant adverse reactions in < 10% of patients receiving BAVENCIO in the JAVELIN Merkel 200 trial were dizziness, headache, transaminase increased, creatine phosphokinase increased, and tubulointerstitial nephritis.

Table 4: Laboratory Abnormalities Worsening from Baseline Occurring in ≥ 20% of Patients with Metastatic MCC Receiving BAVENCIO in the JAVELIN Merkel 200 Trial
Laboratory Tests | Any Grade % [Each test incidence is based on the number of patients who had both baseline and at least one on-study laboratory measurement available (range: 185 to 199 patients).] | Grade 3-4 %
Hematology
Lymphocyte count decreased | 51 | 16
Hemoglobin decreased | 40 | 6
Platelet count decreased | 23 | 1.5
Chemistry
Aspartate aminotransferase (AST) increased | 31 | 3
Alanine aminotransferase (ALT) increased | 22 | 3.5
Lipase increased | 21 | 5

Locally Advanced or Metastatic Urothelial Carcinoma

First-Line Maintenance Treatment of Urothelial Carcinoma

The safety of BAVENCIO was evaluated in the JAVELIN Bladder 100 trial where patients received BAVENCIO 10 mg/kg every 2 weeks plus best supportive care (BSC) (N=344) or BSC alone (N=345). Patients with autoimmune diseases or conditions requiring systemic immunosuppression were excluded.

In the BAVENCIO plus BSC arm, 47% were exposed to BAVENCIO for > 6 months and 28% were exposed for > 1 year [see Clinical Studies (14.2)].

The median age of patients treated with BAVENCIO plus BSC was 69 years (range: 37 to 90), 63% of patients were 65 years or older, 76% were male, 67% were White, and the ECOG performance score was 0 (61%) or 1 (39%).

A fatal adverse reaction (sepsis) occurred in one (0.3%) patient receiving BAVENCIO plus BSC.

Serious adverse reactions occurred in 28% of patients receiving BAVENCIO plus BSC. Serious adverse reactions in ≥ 1% of patients included urinary tract infection (including kidney infection, pyelonephritis, and urosepsis) (6.1%), pain (including abdominal, back, bone, flank, extremity, and pelvic pain) (3.2%), acute kidney injury (1.7%), hematuria (1.5%), sepsis (1.2%), and infusion-related reaction (1.2%).

Permanent discontinuation due to an adverse reaction of BAVENCIO plus BSC occurred in 12% of patients. Adverse reactions resulting in permanent discontinuation of BAVENCIO in > 1% of patients were myocardial infarction (including acute myocardial infarction and troponin T increased) (1.5%) and infusion-related reaction (1.2%).

Dose interruptions due to an adverse reaction, excluding temporary interruptions of BAVENCIO infusions due to infusion-related reactions, occurred in 41% of patients receiving BAVENCIO plus BSC. Adverse reactions leading to interruption of BAVENCIO in > 2% of patients were urinary tract infection (including pyelonephritis) (4.7%) and blood creatinine increased (including acute kidney injury, renal impairment, and renal failure) (3.8%).

The most common adverse reactions (≥ 20%) in patients receiving BAVENCIO plus BSC were fatigue, musculoskeletal pain, urinary tract infection, and rash.

Thirty-one (9%) patients treated with BAVENCIO plus BSC received an oral prednisone dose equivalent to ≥ 40 mg daily for an immune-mediated adverse reaction [see Warnings and Precautions (5)].

Table 5 summarizes adverse reactions that occurred in ≥ 10% of patients treated with BAVENCIO plus BSC.

Table 5: Adverse Reactions (≥ 10%) of Patients Receiving BAVENCIO plus BSC (JAVELIN Bladder 100 Trial)
Adverse Reactions | BAVENCIO plus BSC (N=344) |  | BSC (N=345)
Adverse Reactions | All Grades % | Grade 3-4 % | All Grades % | Grade 3-4 %
General Disorders and Administration Site Conditions
Fatigue [Fatigue is a composite term that includes fatigue, asthenia and malaise.] | 35 | 1.7 | 13 | 1.7
Pyrexia | 15 | 0.3 | 3.5 | 0
Musculoskeletal and Connective Tissue Disorders
Musculoskeletal pain [Musculoskeletal pain is a composite term that includes musculoskeletal pain, back pain, myalgia, and neck pain.] | 24 | 1.2 | 15 | 2.6
Arthralgia | 16 | 0.6 | 6 | 0
Skin and Subcutaneous Tissue Disorders
Rash [Rash is a composite term that includes rash, rash maculo-papular, erythema, dermatitis acneiform, eczema, erythema multiforme, rash erythematous, rash macular, rash papular, rash pruritic, drug eruption and lichen planus.] | 20 | 1.2 | 2.3 | 0
Pruritus | 17 | 0.3 | 1.7 | 0
Infections and Infestations
Urinary tract infection [Urinary tract infection is a composite term that includes urinary tract infection, urosepsis, cystitis, kidney infection, pyuria, pyelonephritis, bacteriuria, pyelonephritis acute, urinary tract infection bacterial, and Escherichia urinary tract infection.] | 20 | 6 | 11 | 3.8
Gastrointestinal Disorders
Diarrhea | 17 | 0.6 | 4.9 | 0.3
Constipation | 16 | 0.6 | 9.0 | 0
Nausea | 16 | 0.3 | 6 | 0.6
Vomiting | 13 | 1.2 | 3.5 | 0.6
Respiratory, Thoracic and Mediastinal Disorders
Cough [Cough is a composite term that includes cough and productive cough.] | 14 | 0.3 | 4.6 | 0
Metabolism and Nutrition Disorders
Decreased appetite | 14 | 0.3 | 7 | 0.6
Endocrine disorders
Hypothyroidism | 12 | 0.3 | 0.6 | 0
Injury, Poisoning and Procedural Complications
Infusion-related reaction | 10 | 0.9 | 0 | 0

Patients received pre-medication with an anti-histamine and acetaminophen prior to each infusion. Infusion-related reactions occurred in 10% (Grade 3: 0.9%) of patients treated with BAVENCIO plus BSC.

Table 6: Selected Laboratory Abnormalities Worsening from Baseline Occurring in ≥ 10% of Patients Receiving BAVENCIO plus BSC (JAVELIN Bladder 100 Trial)
Laboratory Abnormality | BAVENCIO plus BSC [Each test incidence is based on the number of patients who had both baseline and at least one on-study laboratory measurement available: BAVENCIO plus BSC group (range: 339 to 344 patients) and BSC group (range: 329 to 341 patients).] |  | BSC
Laboratory Abnormality | Any Grade % | Grade 3-4 % | Any Grade % | Grade 3-4 %
Chemistry
Blood triglycerides increased | 34 | 2.1 | 28 | 1.2
Alkaline phosphatase increased | 30 | 2.9 | 20 | 2.3
Blood sodium decreased | 28 | 6 | 20 | 2.6
Lipase increased | 25 | 8 | 16 | 6
Aspartate aminotransferase (AST) increased | 24 | 1.7 | 12 | 0.9
Blood potassium increased | 24 | 3.8 | 16 | 0.9
Alanine aminotransferase (ALT) increased | 24 | 2.6 | 12 | 0.6
Blood cholesterol increased | 22 | 1.2 | 16 | 0.3
Serum amylase increased | 21 | 5 | 12 | 1.8
CPK increased | 19 | 2.4 | 12 | 0
Phosphate decreased | 19 | 3.2 | 15 | 1.2
Hematology
Hemoglobin decreased | 28 | 4.4 | 18 | 3.2
White blood cell decreased | 20 | 0.6 | 10 | 0
Platelet count decreased | 18 | 0.6 | 12 | 0.3

Previously-treated Urothelial Carcinoma

The safety of BAVENCIO was evaluated in 242 patients with locally advanced or metastatic UC receiving BAVENCIO at 10 mg/kg every 2 weeks in the UC cohorts of the JAVELIN Solid Tumor trial. Patients received pre-medication with an anti-histamine and acetaminophen prior to each infusion. The median duration of exposure to BAVENCIO was 12 weeks (range: 2 weeks to 92 weeks) [see Clinical Studies (14.2)].

Fourteen patients (6%) who were treated with BAVENCIO experienced either pneumonitis, respiratory failure, sepsis/urosepsis, cerebrovascular accident, or gastrointestinal adverse events, which led to death.

Grade 1-4 serious adverse reactions were reported in 41% of patients. The most frequent serious adverse reactions reported in ≥ 2% of patients were urinary tract infection/urosepsis, abdominal pain, musculoskeletal pain, creatinine increased/renal failure, dehydration, hematuria/urinary tract hemorrhage, intestinal obstruction/small intestine obstruction, and pyrexia.

Permanent discontinuation due to an adverse reaction for BAVENCIO occurred in 12% of patients. The adverse reaction that resulted in permanent discontinuation in > 1% of patients was fatigue.

Dose interruptions due to an adverse reaction, excluding temporary interruptions due to infusion-related reactions, occurred in 29% of patients receiving BAVENCIO. Adverse reactions leading to interruption of BAVENCIO in > 1% of patients were diarrhea, fatigue, dyspnea, urinary tract infection, and rash.

The most common Grade 3 and 4 adverse reactions (≥ 3%) were anemia, fatigue, hyponatremia, hypertension, urinary tract infection, and musculoskeletal pain.

The most common adverse reactions (≥ 20%) were fatigue, infusion-related reaction, musculoskeletal pain, nausea, decreased appetite, and urinary tract infection.

Eleven (4.5%) patients received an oral prednisone dose equivalent to ≥ 40 mg daily for an immune-mediated adverse reaction [see Warnings and Precautions (5)].

Advanced Renal Cell Carcinoma

The safety of BAVENCIO was evaluated in JAVELIN Renal 101. Patients with autoimmune disease other than type I diabetes mellitus, vitiligo, psoriasis, or thyroid disorders not requiring immunosuppressive treatment were excluded. Patients received BAVENCIO 10 mg/kg every 2 weeks administered in combination with axitinib 5 mg twice daily (N=434) or sunitinib 50 mg once daily for 4 weeks followed by 2 weeks off (N=439).

In the BAVENCIO plus axitinib arm, 70% were exposed to BAVENCIO for ≥ 6 months and 29% were exposed for ≥ 1 year in JAVELIN Renal 101 [see Clinical Studies (14.3)].

The median age of patients treated with BAVENCIO in combination with axitinib was 62 years (range: 29 to 83), 38% of patients were 65 years or older, 71% were male, 75% were White, and the ECOG performance score was 0 (64%) or 1 (36%).

Fatal adverse reactions occurred in 1.8% of patients receiving BAVENCIO in combination with axitinib. These included sudden cardiac death (1.2%), stroke (0.2%), myocarditis (0.2%), and necrotizing pancreatitis (0.2%).

Serious adverse reactions occurred in 35% of patients receiving BAVENCIO in combination with axitinib. Serious adverse reactions in ≥ 1% of patients included diarrhea (2.5%), dyspnea (1.8%), hepatotoxicity (1.8%), venous thromboembolic disease (1.6%), acute kidney injury (1.4%), and pneumonia (1.2%).

Permanent discontinuation due to an adverse reaction of either BAVENCIO or axitinib occurred in 22% of patients: 19% BAVENCIO only, 13% axitinib only, and 8% both drugs. The most common adverse reactions (> 1%) resulting in permanent discontinuation of BAVENCIO or the combination were hepatotoxicity (6%) and infusion-related reaction (1.8%).

Dose interruptions or reductions due to an adverse reaction, excluding temporary interruptions of BAVENCIO infusions due to infusion-related reactions, occurred in 76% of patients receiving BAVENCIO in combination with axitinib. This includes interruption of BAVENCIO in 50% of patients. Axitinib was interrupted in 66% and dose reduced in 19% of patients. The most common adverse reaction (> 10%) resulting in interruption of BAVENCIO was diarrhea (10%) and the most common adverse reactions resulting in either interruption or dose reduction of axitinib were diarrhea (19%), hypertension (18%), palmar-plantar erythrodysesthesia (18%), and hepatotoxicity (10%).

The most common adverse reactions (≥ 20%) in patients receiving BAVENCIO in combination with axitinib were diarrhea, fatigue, hypertension, musculoskeletal pain, nausea, mucositis, palmar-plantar erythrodysesthesia, dysphonia, decreased appetite, hypothyroidism, rash, hepatotoxicity, cough, dyspnea, abdominal pain, and headache.

Forty-eight (11%) patients treated with BAVENCIO in combination with axitinib received an oral prednisone dose equivalent to ≥ 40 mg daily for an immune-mediated adverse reaction [see Warnings and Precautions (5)].

Table 7 summarizes adverse reactions that occurred in ≥ 20% of BAVENCIO in combination with axitinib-treated patients.

Table 7: Adverse Reactions (≥ 20%) of Patients Receiving BAVENCIO in Combination with Axitinib (JAVELIN Renal 101 Trial)
Adverse Reactions | BAVENCIO plus Axitinib (N=434) |  | Sunitinib (N=439)
Adverse Reactions | All Grades % | Grade 3-4 % | All Grades % | Grade 3-4 %
Gastrointestinal Disorders
Diarrhea [Diarrhea is a composite term that includes diarrhea, autoimmune colitis, and colitis.] | 62 | 8 | 48 | 2.7
Nausea | 34 | 1.4 | 39 | 1.6
Mucositis [Mucositis is a composite term that includes mucosal inflammation and stomatitis.] | 34 | 2.8 | 35 | 2.1
Hepatotoxicity [Hepatotoxicity is a composite term that includes ALT increased, AST increased, autoimmune hepatitis, bilirubin conjugated, bilirubin conjugated increased, blood bilirubin increased, drug-induced liver injury, hepatic enzyme increased, hepatic function abnormal, hepatitis, hepatitis fulminant, hepatocellular injury, hepatotoxicity, hyperbilirubinemia, immune-mediated hepatitis, liver function test increased, liver disorder, liver injury, and transaminases increased.] | 24 | 9 | 18 | 3.6
Abdominal pain [Abdominal pain is a composite term that includes abdominal pain, flank pain, abdominal pain upper, and abdominal pain lower.] | 22 | 1.4 | 19 | 2.1
General Disorders and Administration Site Conditions
Fatigue [Fatigue is a composite term that includes fatigue and asthenia.] | 53 | 6 | 54 | 6
Vascular Disorders
Hypertension [Hypertension is a composite term that includes hypertension and hypertensive crisis.] | 50 | 26 | 36 | 17
Musculoskeletal and Connective Tissue Disorders
Musculoskeletal pain [Musculoskeletal pain is a composite term that includes musculoskeletal pain, musculoskeletal chest pain, myalgia, back pain, bone pain, musculoskeletal discomfort, neck pain, spinal pain, and pain in extremity.] | 40 | 3.2 | 33 | 2.7
Skin and Subcutaneous Tissue Disorders
Palmar-plantar erythrodysesthesia | 33 | 6 | 34 | 4
Rash [Rash is a composite term that includes rash, rash generalized, rash macular, rash maculo-papular, rash pruritic, rash erythematous, rash papular, and rash pustular.] | 25 | 0.9 | 16 | 0.5
Respiratory, Thoracic and Mediastinal Disorders
Dysphonia | 31 | 0.5 | 3.2 | 0
Dyspnea [Dyspnea is a composite term that includes dyspnea, dyspnea exertional and dyspnea at rest.] | 23 | 3 | 16 | 1.8
Cough | 23 | 0.2 | 19 | 0
Metabolism and Nutrition Disorders
Decreased appetite | 26 | 2.1 | 29 | 0.9
Endocrine Disorders
Hypothyroidism | 25 | 0.2 | 14 | 0.2
Nervous System Disorders
Headache | 21 | 0.2 | 16 | 0.2

Other clinically important adverse reactions that occurred in less than 20% of patients in JAVELIN Renal 101 included arthralgia, weight decreased, and chills.

Patients received pre-medication with an anti-histamine and acetaminophen prior to each infusion. Infusion-related reactions occurred in 12% (Grade 3: 1.6%; no Grade 4) of patients treated with BAVENCIO in combination with axitinib.

Table 8 summarizes selected laboratory abnormalities that occurred in ≥ 20% of BAVENCIO in combination with axitinib-treated patients.

Table 8: Selected Laboratory Abnormalities Worsening from Baseline Occurring in ≥ 20% of Patients Receiving BAVENCIO in Combination with Axitinib (JAVELIN Renal 101 Trial)
Laboratory Abnormality | BAVENCIO plus Axitinib [Each test incidence is based on the number of patients who had both baseline and at least one on-study laboratory measurement available: BAVENCIO in combination with axitinib group (range: 413 to 428 patients) and sunitinib group (range: 405 to 433 patients).] |  | Sunitinib
Laboratory Abnormality | Any Grade % | Grade 3-4 % | Any Grade % | Grade 3-4 %
Chemistry
Blood triglycerides increased | 71 | 13 | 48 | 5
Blood creatinine increased | 62 | 2.3 | 68 | 1.4
Blood cholesterol increased | 57 | 1.9 | 22 | 0.7
Alanine aminotransferase increased (ALT) | 50 | 9 | 46 | 3.2
Aspartate aminotransferase increased (AST) | 47 | 7 | 57 | 3.2
Blood sodium decreased | 38 | 9 | 37 | 10
Lipase increased | 37 | 14 | 25 | 7
Blood potassium increased | 35 | 3 | 28 | 3.9
Blood bilirubin increased | 21 | 1.4 | 23 | 1.4
Hematology
Platelet count decreased | 27 | 0.7 | 80 | 15
Hemoglobin decreased | 21 | 2.1 | 65 | 8

6.2 Postmarketing Experience

The following adverse reactions have been identified during postapproval use of BAVENCIO. Because these reactions are reported voluntarily from a population of uncertain size, it is not always possible to reliably estimate their frequency or establish a causal relationship to drug exposure.

Blood and lymphatic system disorders: neutropenia

Hepatobiliary disorders: sclerosing cholangitis

8 USE IN SPECIFIC POPULATIONS

8.1 Pregnancy

Risk Summary

Based on its mechanism of action, BAVENCIO can cause fetal harm when administered to a pregnant woman. There are no available data on the use of BAVENCIO in pregnant women [see Clinical Pharmacology (12.1)]. Animal studies have demonstrated that inhibition of the PD-1/PD-L1 pathway can lead to increased risk of immune-mediated rejection of the developing fetus resulting in fetal death [see Data]. Human IgG1 immunoglobulins (IgG1) are known to cross the placenta. Therefore, BAVENCIO has the potential to be transmitted from the mother to the developing fetus. If this drug is used during pregnancy, or if the patient becomes pregnant while taking this drug, advise the patient of the potential risk to a fetus.

In the U.S. general population, the estimated background risk of major birth defects and miscarriage in clinically recognized pregnancies is 2% to 4% and 15% to 20%, respectively.

Data

Animal Data

Animal reproduction studies have not been conducted with BAVENCIO to evaluate its effect on reproduction and fetal development. A central function of the PD-1/PD-L1 pathway is to preserve pregnancy by maintaining maternal immune tolerance to the fetus. In murine models of pregnancy, blockade of PD-L1 signaling has been shown to disrupt tolerance to the fetus and to result in an increase in fetal loss; therefore, potential risks of administering BAVENCIO during pregnancy include increased rates of abortion or stillbirth. As reported in the literature, there were no malformations related to the blockade of PD-1/PD-L1 signaling in the offspring of these animals; however, immune-mediated disorders occurred in PD-1 and PD-L1 knockout mice. Based on its mechanism of action, fetal exposure to BAVENCIO may increase the risk of developing immune-mediated disorders or altering the normal immune response.

8.2 Lactation

Risk Summary

There is no information regarding the presence of avelumab in human milk, the effects on the breastfed infant, or the effects on milk production. Since many drugs including antibodies are excreted in human milk, advise a lactating woman not to breastfeed during treatment and for at least one month after the last dose of BAVENCIO due to the potential for serious adverse reactions in breastfed infants.

8.3 Females and Males of Reproductive Potential

Contraception

Based on its mechanism of action, BAVENCIO can cause fetal harm when administered to a pregnant woman [see Use in Specific Populations (8.1)]. Advise females of reproductive potential to use effective contraception during treatment with BAVENCIO and for at least 1 month after the last dose of BAVENCIO.

8.4 Pediatric Use

The safety and effectiveness of BAVENCIO have been established in pediatric patients aged 12 years and older for metastatic MCC. Use of BAVENCIO in this age group is supported by evidence from adequate and well-controlled studies of BAVENCIO in adults with additional population pharmacokinetic data demonstrating that age and body weight had no clinically meaningful effect on the steady state exposure of avelumab, that drug exposure is generally similar between adults and pediatric patients age 12 years and older for monoclonal antibodies, and that the course of MCC is sufficiently similar in adult and pediatric patients to allow extrapolation of data in adults to pediatric patients. The recommended dose in pediatric patients 12 years of age or greater is the same as that in adults [see Dosage and Administration (2.2), Clinical Pharmacology (12.3), and Clinical Studies (14)].

Safety and effectiveness of BAVENCIO have not been established in pediatric patients less than 12 years of age.

8.5 Geriatric Use

Metastatic Merkel Cell Carcinoma

Of the 204 patients with MCC who received BAVENCIO in the JAVELIN Merkel 200 trial, 78% were 65 years or older and 43% were 75 years or older. No overall differences in safety or efficacy were observed between elderly patients and younger patients.

Locally Advanced or Metastatic Urothelial Carcinoma

Of the 344 patients randomized to BAVENCIO 10 mg/kg plus BSC in the JAVELIN Bladder 100 trial, 63% were 65 years or older and 24% were 75 years or older. No overall differences in safety or efficacy were reported between elderly patients and younger patients.

Advanced Renal Cell Carcinoma

Of the 434 patients randomized to BAVENCIO 10 mg/kg administered in combination with axitinib 5 mg twice daily in the JAVELIN Renal 101 trial, 38% were 65 years or older and 8% were 75 years or older. No overall difference in safety or efficacy were reported between elderly patients and younger patients.

11 DESCRIPTION

Avelumab is a programmed death ligand1 (PD-L1) blocking antibody. Avelumab is a human IgG1 lambda monoclonal antibody produced in Chinese hamster ovary cells and has a molecular weight of approximately 147 kDa.

BAVENCIO (avelumab) Injection for intravenous use is a sterile, preservative-free, non-pyrogenic, clear, colorless to slightly yellow solution. Each single-dose vial contains 200 mg avelumab in 10 mL (20 mg/mL). Each mL contains 20 mg avelumab, D-mannitol (51 mg), glacial acetic acid (0.6 mg), polysorbate 20 (0.5 mg), sodium hydroxide (0.3 mg), and Water for Injection. The pH range of the solution is 5.0 – 5.6.

12 CLINICAL PHARMACOLOGY

12.1 Mechanism of Action

PD-L1 may be expressed on tumor cells and tumor-infiltrating immune cells and can contribute to the inhibition of the anti-tumor immune response in the tumor microenvironment. Binding of PD-L1 to the PD-1 and B7.1 receptors found on T cells and antigen presenting cells suppresses cytotoxic T-cell activity, T-cell proliferation, and cytokine production. Avelumab binds PD-L1 and blocks the interaction between PD-L1 and its receptors PD-1 and B7.1. This interaction releases the inhibitory effects of PD-L1 on the immune response resulting in the restoration of immune responses, including anti-tumor immune responses. Avelumab has also been shown to induce antibody-dependent cell-mediated cytotoxicity (ADCC) in vitro. In syngeneic mouse tumor models, blocking PD-L1 activity resulted in decreased tumor growth.

12.2 Pharmacodynamics

Avelumab exposure-response relationships and the time course of pharmacodynamic response are not fully characterized.

12.3 Pharmacokinetics

The pharmacokinetics (PK) of avelumab as a single agent was characterized in patients who received BAVENCIO at doses ranging from 1 to 20 mg/kg every 2 weeks (0.1 to 2 times of the approved recommended dosage). The exposure of avelumab increased dose-proportionally from 10 to 20 mg/kg every 2 weeks. Steady-state concentrations of avelumab were reached after approximately 4 to 6 weeks (2 to 3 cycles) and the systemic accumulation was 1.25-fold.

Distribution

The mean volume of distribution at steady state after patients received a dose of 10 mg/kg was 4.7 L (coefficient of variation (% CV) of 44%).

Elimination

The primary elimination mechanism of avelumab is proteolytic degradation.

The total systemic clearance (% CV) was 0.59 L/day (25%) and the terminal half-life (% CV) was 6.1 days (92%) in patients who received a dose of 10 mg/kg every 2 weeks. Avelumab clearance decreased over time in patients with MCC, with a mean maximal reduction (CV%) from baseline value of approximately 32% (36%), which is not considered clinically important. A change of avelumab clearance over time was not observed in patients with UC or with RCC.

Specific Populations

No clinically meaningful differences in pharmacokinetics were observed in the clearance of avelumab based on age; body weight; sex; race; PD-L1 status; tumor burden; mild to severe renal impairment (calculated creatinine clearance of 89 to 15 mL/min, as estimated by the Cockcroft-Gault formula), and mild or moderate hepatic impairment (bilirubin less than or equal to 3 times ULN). The effect of severe hepatic impairment (bilirubin greater than 3 times ULN) on the pharmacokinetics of avelumab is unknown.

Drug Interactions

BAVENCIO with axitinib: Avelumab PK was assessed following administration of BAVENCIO in combination with axitinib. There are no clinically meaningful differences in exposure of avelumab when administered in combination with axitinib.

12.6 Immunogenicity

The observed incidence of anti-drug antibodies (ADA) is highly dependent on the sensitivity and specificity of the assay. Differences in assay methods preclude meaningful comparisons of the incidence of ADA in the studies described below with the incidence of ADA in other studies, including those of BAVENCIO or of other avelumab products.

ADA responses following administration of BAVENCIO 10 mg/kg every 2 weeks were evaluated during the respective treatment periods in each trial. The ADA and neutralizing antibody (nAb) incidences are listed in Table 9.

Table 9: BAVENCIO ADA Incidence
Trial Name [Details of each treatment regimen are described in Section 14 [see Clinical Studies (14)].] | Treatment Period (months) | ADA | nAb
JAVELIN Merkel 200 Part A | 48 | 8.9% (7/79) | 71% (5/7)
JAVELIN Merkel 200 Part B | 35 | 8.2% (9/110) | 89% (8/9)
JAVELIN Bladder 100 | 37 | 19% (62/326) | 97% (60/62)
JAVELIN Solid Tumor, UC Cohort | 59 | 18% (41/226) | Not tested
JAVELIN Renal 101 | 29 | 16% (65/411) | 78% (51/65)
ADA: anti-avelumab antibodies; UC: urothelial carcinoma

In patients with advanced UC or advanced RCC, avelumab clearance was approximately 15% higher in patients who tested positive for ADA as compared to clearance in patients who tested negative for ADA; which is not considered clinically meaningful. The effect of ADA on the efficacy or safety could not be determined due to the low occurrence of ADAs.

13 NONCLINICAL TOXICOLOGY

13.1 Carcinogenesis, Mutagenesis, Impairment of Fertility

No studies have been conducted to assess the potential of avelumab for genotoxicity or carcinogenicity.

Fertility studies have not been conducted with avelumab; however, an assessment of male and female reproductive organs was included in 3-month repeat-dose toxicity study in Cynomolgus monkeys. Weekly administration of avelumab did not result in any notable effects in the male and female reproductive organs.

13.2 Animal Toxicology and/or Pharmacology

In animal models, inhibition of PD-L1/PD-1 signaling increased the severity of some infections and enhanced inflammatory responses. M. tuberculosis-infected PD-1 knockout mice exhibit markedly decreased survival compared with wild-type controls, which correlated with increased bacterial proliferation and inflammatory responses in these animals. PD-L1 and PD-1 knockout mice and mice receiving PD-L1 blocking antibody have also shown decreased survival following infection with lymphocytic choriomeningitis virus.

14 CLINICAL STUDIES

14.1 Metastatic Merkel Cell Carcinoma

The efficacy and safety of BAVENCIO was demonstrated in the JAVELIN Merkel 200 trial (NCT02155647), an open-label, single--arm, multi-center study conducted in patients with histologically confirmed metastatic MCC. This trial consisted of two parts; Part A enrolled patients with metastatic MCC whose disease had progressed on or after chemotherapy administered for distant metastatic disease, and Part B enrolled patients with metastatic MCC who were treatment-naïve. The trial excluded patients with autoimmune disease; medical conditions requiring systemic immunosuppression; prior organ or allogeneic stem cell transplantation; prior treatment with anti-PD-1, anti-PD-L1, or anti-CTLA-4 antibodies; CNS metastases; infection with HIV, hepatitis B, or hepatitis C; or ECOG performance score ≥ 2.

Patients received BAVENCIO 10 mg/kg as an intravenous infusion over 60 minutes every 2 weeks until disease progression or unacceptable toxicity. Patients with radiological disease progression not associated with significant clinical deterioration, defined as no new or worsening symptoms, no change in performance status for greater than 2 weeks, and no need for salvage therapy, could continue treatment. Tumor response assessments were performed every 6 weeks.

The major efficacy outcome measures were confirmed overall response rate (ORR) according to Response Evaluation Criteria in Solid Tumors (RECIST) v1.1 as assessed by a blinded independent central review committee (IRC) and IRC-assessed duration of response.

Previously-treated Merkel Cell Carcinoma

A total of 88 patients were enrolled in Part A. Baseline patient characteristics were a median age of 73 years (range: 33 to 88), 74% of patients were male, 92% were White, and the ECOG performance score was 0 (56%) or 1 (44%). Seventy-five percent of patients were 65 years or older, 35% were 75 or older, and 3% were 85 or older. Sixty-five percent of patients were reported to have had one prior anti-cancer therapy for metastatic MCC and 35% had two or more prior therapies. Fifty-three percent of patients had visceral metastases. Sixty-six percent were PD-L1-positive (≥ 1% of tumor cells), 18% were PD-L1 negative, and 16% had non-evaluable results by an investigational immunohistochemistry assay. Archival tumor samples were evaluated for Merkel cell polyomavirus (MCV) using an investigational assay; of the 77 patients with evaluable results, 52% had evidence of MCV.

Efficacy results are summarized in Table 10. Responses were observed in patients regardless of tumor PD-L1 expression or presence of MCV.

Table 10: Efficacy Results from the JAVELIN Merkel 200 Trial in Previously-Treated Patients with Metastatic MCC (Part A)
Efficacy Endpoints | BAVENCIO (N=88)
Overall Response Rate (ORR)
Overall response rate, n (%) | 29 (33%)
(95% CI) | (23, 44)
Complete responses, n (%) | 10 (11%)
Partial responses, n (%) | 19 (22%)
Duration of Response (DOR) | N=29
Median DOR in months (range) | 40.5 (2.8, 41.5+)
Patients with DOR ≥ 6 months, n (%) | 26 (90%)
Patients with DOR ≥ 12 months, n (%) | 19 (66%)
CI: Confidence interval.

Treatment-naïve Merkel Cell Carcinoma

A total of 116 patients were enrolled in Part B. Baseline patient characteristics were median age of 74 years (range: 41 to 93); 70% of patients were male; 65% were White, 31% were unknown or not collected, 2.6% were Asian, and 1.7% were Black; ECOG performance score was 0 (62%) or 1 (38%). Eighteen percent of patients were PD-L1-positive (≥ 1% of tumor cells), 75% were PD-L1-negative, and 7% had non-evaluable results by an investigational immunohistochemistry assay. Sixty percent of patients had Merkel cell polyomavirus (MCV).

Efficacy results are presented in Table 11. Responses were observed in patients regardless of tumor PD-L1 expression or presence of MCV.

Table 11: Efficacy Results of the JAVELIN Merkel 200 Trial in Patients with Treatment-Naïve Metastatic MCC (Part B)
Efficacy Endpoints | BAVENCIO (N=116)
Overall Response Rate (ORR)
Overall response rate, n (%) | 46 (40%)
(95% CI) | (31, 49)
Complete responses, n (%) | 19 (16%)
Partial responses, n (%) | 27 (23%)
Duration of Response (DOR) | N=46
Median DOR in months, (range) | 18.2 (1.2+, 28.3+)
Patients with DOR ≥ 6 months, n (%) | 35 (76%)
Patients with DOR ≥ 12 months, n (%) | 24 (52%)
CI: Confidence interval.

14.2 Locally Advanced or Metastatic Urothelial Carcinoma

First-Line Maintenance Treatment of Urothelial Carcinoma

The efficacy and safety of BAVENCIO was demonstrated in the JAVELIN Bladder 100 trial (NCT02603432), a randomized, multi-center, open-label study conducted in 700 patients with unresectable, locally advanced or metastatic urothelial carcinoma that did not progress with first-line platinum-containing chemotherapy. Patients with autoimmune disease or a medical condition that required immunosuppression were excluded.

Randomization was stratified by best response to chemotherapy (CR/PR vs. stable disease [SD]) and site of metastasis (visceral vs. non-visceral) at the time of initiating first-line chemotherapy. Patients were randomized (1:1) to receive either BAVENCIO 10 mg/kg intravenous infusion every 2 weeks plus best supportive care (BSC) or BSC alone. Treatment was initiated within 4-10 weeks after the last dose of chemotherapy.

Treatment with BAVENCIO continued until RECIST v1.1-defined progression of disease by Blinded Independent Central Review (BICR) assessment or unacceptable toxicity. Administration of BAVENCIO was permitted beyond RECIST-defined disease progression if the patient was clinically stable and was considered to be deriving clinical benefit by the investigator. Assessment of tumor status was performed at baseline, 8 weeks after randomization, then every 8 weeks up to 12 months after randomization, and every 12 weeks thereafter until documented confirmed disease progression based on BICR assessment per RECIST v1.1.

Baseline characteristics were well-balanced between arms. Overall, the median age was 69 years (range: 32 to 90), with 66% of patients ≥ 65 years of age and 24% of patients ≥ 75 years of age. Most patients were male (77%). The majority of patients were White (67%) and 22% were Asian. Baseline ECOG PS was 0 (61%) or 1 (39%).

Fifty-six percent (56%) of patients received prior gemcitabine plus cisplatin, 38% of patients received prior gemcitabine plus carboplatin, and 6% of patients received prior gemcitabine plus cisplatin and gemcitabine plus carboplatin. Best response to first-line chemotherapy was CR or PR (72%) or SD (28%). Sites of metastasis prior to chemotherapy were visceral (55%) or non-visceral (45%). Fifty-one (51%) of patients had PD-L1-positive-tumors, 39% of patients had PD-L1-negative tumors, and 10% of patients had unknown PD-L1 tumor status. Six percent (6%) of patients received another PD-1/PD-L1 checkpoint inhibitor after discontinuation of treatment in the BAVENCIO plus BSC arm and 44% of patients in the BSC arm.

The major efficacy outcome measure was overall survival (OS) in all randomized patients and patients with PD-L1-positive tumors. The results from a pre-specified interim analysis demonstrated a statistically significant improvement in OS for patients randomized to BAVENCIO plus BSC as compared with BSC alone. An updated OS analysis was conducted when 452 deaths were observed. Consistent results were observed across the pre-specified subgroups of CR/PR versus SD to first-line chemotherapy.

Table 12: Efficacy Results from the JAVELIN Bladder 100 Trial
Efficacy Endpoints | BAVENCIO plus BSC | BSC
 | (N=350) | (N=350)
Primary OS
Events (%) | 145 (41.4) | 179 (51.1)
Median in months | 21.4 | 14.3
(95% CI) | (18.9, 26.1) | (12.9, 17.9)
Hazard ratio (95% CI) | 0.69 (0.56, 0.86)
p-value [p-value based on 2-sided stratified log-rank.] | 0.001
Updated OS
Events (%) | 215 (61.4) | 237 (67.7)
Median in months | 23.8 | 15.0
(95% CI) | (19.9, 28.8) | (13.5, 18.2)
Hazard ratio (95% CI) | 0.76 (0.63, 0.92)
BSC: Best supportive care; CI: Confidence interval; OS: overall survival.

Figure 1: K-M Estimates for Updated OS from the JAVELIN Bladder 100 Trial

In the pre-specified endpoint of OS among patients with PD-L1-positive tumors (n=358, 51%), the hazard ratio was 0.69 (95% CI: 0.52, 0.90) in the updated OS analysis for patients randomized to BAVENCIO plus BSC versus BSC alone. In an exploratory analysis of patients with PD-L1-negative tumors (n=270, 39%), the updated OS hazard ratio was 0.82 (95% CI: 0.62, 1.09).

Previously-treated Urothelial Carcinoma

The efficacy and safety of BAVENCIO was demonstrated in the UC cohorts of the JAVELIN Solid Tumor trial, an open-label, single-arm, multi-center study that included 242 patients with locally advanced or metastatic urothelial carcinoma (UC) with disease progression on or after platinum-containing chemotherapy or who had disease progression within 12 months of treatment with a platinum-containing neoadjuvant or adjuvant chemotherapy regimen. Patients with active or history of central nervous system metastasis; other malignancies within the last 5 years; organ transplant; conditions requiring therapeutic immune suppression; or active infection with HIV, hepatitis B, or hepatitis C were excluded. Patients with autoimmune disease, other than type I diabetes, vitiligo, psoriasis, or thyroid disease that did not require immunosuppressive treatment, were excluded. Patients were included regardless of their PD-L1 status.

Patients received BAVENCIO at a dose of 10 mg/kg intravenously every 2 weeks until radiographic or clinical progression or unacceptable toxicity. Tumor response assessments were performed every 6 weeks. Efficacy outcome measures included confirmed overall response rate (ORR), as assessed by an Independent Endpoint Review Committee (IERC) using Response Evaluation Criteria in Solid Tumors (RECIST) v1.1, and duration of response (DOR). Efficacy was evaluated in patients who were followed for a minimum of both 13 weeks and 6 months at the time of data cut-off.

Baseline demographic and disease characteristics for the 226 patients with a minimum of 13 weeks of follow-up were median age 68 years (range: 30 to 89), 72% male, 80% White, and 34% and 66% of patients had an ECOG performance status 0 and 1, respectively. Forty-four percent of patients had non-bladder urothelial carcinoma including 23% of patients with upper tract disease, and 83% of patients had visceral metastases (baseline target and/or non-target lesions present outside of the lymph nodes). Nine (4%) patients had disease progression following prior platinum-containing neoadjuvant or adjuvant therapy only. Forty-seven percent of patients only received prior cisplatin-based regimens, 32% received only prior carboplatin-based regimens, and 20% received both cisplatin and carboplatin-based regimens. At baseline, 17% of patients had a hemoglobin < 10 g/dL and 34% of patients had liver metastases.

Efficacy results are presented in Table 13. The median time to response was 2.0 months (range: 1.3 to 11.0) among patients followed for either ≥ 13 weeks or ≥ 6 months. Using a clinical trial assay to assess PD-L1 staining, with 16% of patients not evaluable, there were no clear differences in response rates based on PD-L1 tumor expression. Among the total 30 responding patients followed for ≥ 13 weeks, 22 patients (73%) had an ongoing response of 6 months or longer and 4 patients (13%) had ongoing responses of 12 months or longer. Among the total 26 responding patients followed for ≥ 6 months, 22 patients (85%) had ongoing responses of 6 months or longer and 4 patients (15%) had ongoing responses of 12 months or longer.

Table 13: Efficacy Results of the UC Cohorts in the JAVELIN Solid Tumor Trial
Efficacy Endpoints | ≥ 13 Weeks Follow-Up (N=226) | ≥ 6 Months Follow-Up (N=161)
Confirmed Overall Response Rate (ORR)
Overall Response Rate n (%) | 30 (13.3%) | 26 (16.1%)
(95% CI) | (9.1, 18.4) | (10.8, 22.8)
Complete Response (CR) n (%) | 9 (4.0%) | 9 (5.6%)
Partial Response (PR) n (%) | 21 (9.3%) | 17 (10.6%)
Duration of Response (DOR)
Median, months (range) | NE (1.4+ to 17.4+) | NE (1.4+ to 17.4+)
CI: Confidence interval; NE: Not estimable; + denotes a censored value.

14.3 Advanced Renal Cell Carcinoma

The efficacy and safety of BAVENCIO in combination with axitinib was demonstrated in the JAVELIN Renal 101 trial (NCT02684006), a randomized, multicenter, open-label, study of BAVENCIO in combination with axitinib in 886 patients with untreated advanced RCC regardless of tumor PD-L1 expression [intent-to-treat (ITT) population]. Patients with autoimmune disease or conditions requiring systemic immunosuppression were excluded.

Randomization was stratified according to Eastern Cooperative Oncology Group (ECOG) Performance Status (PS) (0 vs. 1) and region (United States vs. Canada/Western Europe vs. the rest of the world). Patients were randomized (1:1) to one of the following treatment arms:

- BAVENCIO 10 mg/kg intravenous infusion every 2 weeks in combination with axitinib 5 mg twice daily orally (N=442). Patients who tolerated axitinib 5 mg twice daily without Grade 2 or greater axitinib-related adverse events for 2 consecutive weeks could increase to 7 mg and then subsequently to 10 mg twice daily. Axitinib could be interrupted or reduced to 3 mg twice daily and subsequently to 2 mg twice daily to manage toxicity.
- Sunitinib 50 mg once daily orally for 4 weeks followed by 2 weeks off (N=444) until radiographic or clinical progression or unacceptable toxicity.

Treatment with BAVENCIO and axitinib continued until RECIST v1.1-defined progression of disease by Blinded Independent Central Review (BICR) assessment or unacceptable toxicity. Administration BAVENCIO and axitinib was permitted beyond RECIST-defined disease progression if the patient was clinically stable and considered to be deriving clinical benefit by the investigator. Assessment of tumor status was performed at baseline, after randomization at 6 weeks, then every 6 weeks thereafter up to 18 months after randomization, and every 12 weeks thereafter until documented confirmed disease progression by BICR.

Baseline characteristics were a median age of 61 years (range: 27 to 88); 38% of patients were 65 years or older; 75% were male; 75% were White, 15% Asian, 2% Black, 1% American Indian or Alaskan Native, 7% unknown; 4% were Hispanic or Latino; ECOG PS was 0 (63%) or 1 (37%); and 63% of patients were PD-L1 positive, 28% were PD-L1 negative, and 8% had unknown PD-L1 status. Patient distribution by International Metastatic Renal Cell Carcinoma Database (IMDC) risk groups was 21% favorable, 62% intermediate, and 16% poor.

The major efficacy outcome measures were progression-free survival (PFS), as assessed by an BICR using RECIST v1.1 and overall survival (OS) in patients with PD-L1-positive tumors using a clinical trial assay (PD-L1 expression level ≥ 1%). PFS was statistically significant in patients with PD-L1-positive tumors [HR 0.61 (95% CI: 0.48, 0.79)] and in the ITT population. The final analysis for OS was not statistically significant for either the PD-L1-positive or ITT population.

Efficacy results for the ITT population are presented in Table 14 and Figure 2.

Table 14: Efficacy Results from JAVELIN Renal 101 Trial - ITT
Efficacy Endpoints | BAVENCIO plus Axitinib (N=442) | Sunitinib (N=444)
Progression-Free Survival (PFS) [Based on BICR assessment.]
Events (%) | 180 (41) | 216 (49)
Median in months (95% CI) | 13.8 (11.1, NE) | 8.4 (6.9, 11.1)
Hazard ratio (95% CI) | 0.69 (0.56, 0.84)
p-value [p-value based on 2-sided stratified log-rank.] | 0.0002
Overall Survival (OS)
Events (%) | 283 (64) | 295 (66)
Median in months (95% CI) | 44.8 (39.7, 51.1) | 38.9 (31.4, 45.2)
Hazard ratio (95% CI) | 0.88 (0.75, 1.04)
p-value | NS
Confirmed Objective Response Rate (ORR)
Objective Response Rate n (%) | 227 (51.4) | 114 (25.7)
(95% CI) | (46.6, 56.1) | (21.7, 30.0)
Complete Response (CR) n (%) | 15 (3.4) | 8 (1.8)
Partial Response (PR) n (%) | 212 (48) | 106 (24)
BICR: Blinded Independent Central Review; CI: Confidence interval; NE: Not estimable; NS: not statistically significant.

Figure 2: K-M Estimates for PFS based on BICR Assessment – ITT

16 HOW SUPPLIED/STORAGE AND HANDLING

BAVENCIO (avelumab) Injection is a sterile, preservative-free, and clear, colorless to slightly yellow solution for intravenous infusion supplied as a single-dose vial of 200 mg/10 mL (20 mg/mL), individually packed into a carton (NDC 44087-3535-1).

STORAGE AND HANDLING

Store refrigerated at 36°F to 46°F (2°C to 8°C) in original package to protect from light.

Do not freeze or shake the vial.

The vial stopper is not made with natural rubber latex.

17 PATIENT COUNSELING INFORMATION

Advise the patient to read the FDA-approved patient labeling (Medication Guide).

Immune-Mediated Adverse Reactions

Inform patients of the risk of immune-mediated adverse reactions requiring corticosteroids or hormone replacement therapy, including, but not limited to:

- Pneumonitis: Advise patients to contact their healthcare provider immediately for new or worsening cough, chest pain, or shortness of breath [see Warnings and Precautions (5.1)].
- Colitis: Advise patients to contact their healthcare provider immediately for diarrhea or severe abdominal pain [see Warnings and Precautions (5.1)].
- Hepatitis: Advise patients to contact their healthcare provider immediately for jaundice, severe nausea or vomiting, pain on the right side of abdomen, lethargy, or easy bruising or bleeding [see Warnings and Precautions (5.1)].
- Endocrinopathies: Advise patients to contact their healthcare provider immediately for signs or symptoms of adrenal insufficiency, hypothyroidism, hyperthyroidism, and diabetes mellitus [see Warnings and Precautions (5.1)].
- Nephritis with Renal Dysfunction: Advise patients to contact their healthcare provider immediately for signs or symptoms of nephritis including decreased urine output, blood in urine, swelling in ankles, loss of appetite, and any other symptoms of renal dysfunction [see Warnings and Precautions (5.1)].
- Dermatologic Adverse Reactions: Advise patients to contact their healthcare provider immediately for signs or symptoms of skin rash, itchy skin, rash with tiny spots and bumps, reddening of skin, blisters or peeling [see Warnings and Precautions (5.1)].

Infusion-Related Reactions

Advise patients to contact their healthcare provider immediately for signs or symptoms of potential infusion-related reactions [see Warnings and Precautions (5.2)].

Complications of Allogeneic HSCT

Advise patients of the risk of post-allogeneic hematopoietic stem cell transplantation complications [see Warnings and Precautions (5.3)].

Major Adverse Cardiovascular Events

Advise patients receiving BAVENCIO in combination with axitinib to contact their healthcare provider immediately for signs or symptoms of cardiovascular events including but not limited to new or worsening chest discomfort, dyspnea, or peripheral edema [see Warnings and Precautions (5.4)].

Embryo-Fetal Toxicity

Advise females of reproductive potential that BAVENCIO can cause fetal harm. Instruct females of reproductive potential to use effective contraception during and for at least one month after the last dose of BAVENCIO [see Warnings and Precautions (5.5) and Use in Specific Populations (8.1, 8.3)].

Lactation

Advise nursing mothers not to breastfeed while taking BAVENCIO and for at least one month after the final dose [see Use in Specific Populations (8.2)].

Manufactured by:
EMD Serono, Inc.
Boston, MA 02210
U.S.A.

Marketed by:
EMD Serono, Inc., MA, USA

US License No: 1773

BAVENCIO is a trademark of Merck KGaA, Darmstadt, Germany

Product of Switzerland

MEDICATION GUIDE
BAVENCIO® (buh-VEN-see-oh)
(avelumab)
injection

What is the most important information I should know about BAVENCIO?
BAVENCIO is a medicine that may treat certain cancers by working with your immune system. BAVENCIO can cause your immune system to attack normal organs and tissues in any area of your body and can affect the way they work. These problems can sometimes become severe or life-threatening and can lead to death. You can have more than one of these problems at the same time. These problems may happen anytime during treatment or even after your treatment has ended.
Call or see your healthcare provider right away if you get any new or worsening signs or symptoms, including:
Lung problems.

- cough

- shortness of breath

- chest pain

Intestinal problems.

- diarrhea (loose stools) or more frequent bowel movements than usual
- stools that are black, tarry, sticky, or have blood or mucus
- severe stomach-area (abdomen) pain or tenderness

Liver problems.

- yellowing of your skin or the whites of your eyes
- severe nausea or vomiting
- pain on the right side of your stomach-area (abdomen)

- dark urine (tea colored)
- bleeding or bruising more easily than normal

Hormone gland problems.

- headache that will not go away or unusual headaches
- eye sensitivity to light
- eye problems
- rapid heartbeat
- increased sweating
- extreme tiredness
- weight gain or weight loss
- feeling more hungry or thirsty than usual

- urinating more often than usual
- hair loss
- feeling cold
- constipation
- your voice gets deeper
- dizziness or fainting
- changes in mood or behavior, such as decreased sex drive, irritability, or forgetfulness

Kidney problems.

- decrease in your amount of urine
- blood in your urine

- swelling of your ankles
- loss of appetite

Skin problems.

- rash
- itching
- skin blistering or peeling

- painful sores or ulcers in mouth or nose, throat, or genital area
- fever or flu-like symptoms
- swollen lymph nodes

Problems can also happen in other organs and tissues. These are not all of the signs or symptoms of immune system problems that can happen with BAVENCIO. Call or see your healthcare provider right away for any new or worsening signs or symptoms, which may include:

- chest pain, irregular heartbeat, shortness of breath or swelling of ankles
- confusion, sleepiness, memory problems, changes in mood or behavior, stiff neck, balance problems, tingling or numbness of the arms or legs
- double vision, blurry vision, sensitivity to light, eye pain, changes in eyesight
- persistent or severe muscle pain or weakness, muscle cramps
- low red blood cells, bruising

Infusion-related reactions can sometimes be severe or life-threatening. Signs and symptoms of infusion-related reactions may include:

- chills or shaking
- hives
- flushing
- shortness of breath or wheezing

- dizziness
- feel like passing out
- fever
- back pain
- stomach area (abdomen) pain

Complications, including graft-versus-host-disease (GVHD), in people who have received a bone marrow (stem cell) transplant that uses donor stem cells (allogeneic). These complications can be serious and can lead to death. These complications may happen if you underwent transplantation either before or after being treated with BAVENCIO. Your healthcare provider will monitor you for these complications.
Heart problems. When BAVENCIO is used with the medicine axitinib, severe heart problems can happen and can lead to death. Signs and symptoms of heart problems may include:

- swelling of your stomach area (abdomen), legs, hands, feet, or ankles
- shortness of breath
- nausea or vomiting
- new or worsening chest discomfort, including pain or pressure

- weight gain
- pain or discomfort in your arms, back, neck, or jaw
- breaking out in a cold sweat
- feeling lightheaded or dizzy

Getting medical treatment right away may help keep these problems from becoming more serious. Your healthcare provider will check you for these problems during your treatment with BAVENCIO. Your healthcare provider may treat you with corticosteroid or hormone replacement medicines. Your healthcare provider may also need to delay or completely stop treatment with BAVENCIO if you have severe side effects.

What is BAVENCIO?
BAVENCIO is a prescription medicine used to treat:

- a type of skin cancer called Merkel cell carcinoma (MCC) in adults and children 12 years of age and older. BAVENCIO may be used when your skin cancer has spread.
- a type of cancer in the bladder or urinary tract called urothelial carcinoma (UC) when it has spread or cannot be removed by surgery (advanced UC). BAVENCIO may be used:
  - as maintenance treatment when your cancer has responded or stabilized after you have received platinum-containing chemotherapy as your first treatment.
  - when you have received platinum-containing chemotherapy, and it did not work or is no longer working.
- a type of kidney cancer called renal cell carcinoma (RCC). BAVENCIO may be used with the medicine axitinib as your first treatment when your kidney cancer has spread or cannot be removed by surgery (advanced RCC).

It is not known if BAVENCIO is safe and effective in children under the age of 12.

Before you receive BAVENCIO, tell your healthcare provider about all of your medical conditions, including if you:

- have immune system problems such as Crohn's disease, ulcerative colitis, or lupus
- have received an organ transplant
- have received or plan to receive a stem cell transplant that uses donor stem cells (allogeneic)
- have a condition that affects your nervous system, such as myasthenia gravis or Guillain-Barré syndrome
- have heart problems or high blood pressure
- have diabetes
- have a high cholesterol level in your blood
- are pregnant or plan to become pregnant. BAVENCIO can harm your unborn baby.
  Females who are able to become pregnant:
  - You should use an effective method of birth control during your treatment and for at least 1 month after the last dose of BAVENCIO. Talk to your healthcare provider about birth control methods that you can use during this time.
- are breastfeeding or plan to breastfeed. It is not known if BAVENCIO passes into your breast milk. Do not breastfeed during treatment and for at least 1 month after the last dose of BAVENCIO.

Tell your healthcare provider about all the medicines you take, including prescription and over-the-counter medicines, vitamins, and herbal supplements.

How will I receive BAVENCIO?

- Your healthcare provider will give you BAVENCIO into your vein through an intravenous (IV) line over 60 minutes.
- BAVENCIO is usually given every 2 weeks.
- Your healthcare provider will give you medicines before the first 4 infusions and then as needed to help reduce infusion reactions.
- Your healthcare provider will decide how many treatments you need.
- Your healthcare provider will do blood tests to check you for certain side effects.
- If you miss an appointment, call your healthcare provider as soon as possible to reschedule your appointment.

What are the possible side effects of BAVENCIO?
BAVENCIO can cause serious side effects, including:

- See "What is the most important information I should know about BAVENCIO?"

The most common side effects of BAVENCIO in people with MCC include:

- feeling tired
- muscle and bone pain
- infusion-related reactions including chills, fever, and back pain
- rash

- nausea
- constipation
- cough
- diarrhea

The most common side effects of BAVENCIO as maintenance treatment in people with UC whose cancer responded or stabilized after platinum-containing chemotherapy as first treatment include:

- feeling tired
- muscle and bone pain

- urinary tract infection
- rash

The most common side effects of BAVENCIO in people with UC after platinum-containing chemotherapy that did not work, or is no longer working, include:

- feeling tired
- infusion-related reactions including chills, fever, back pain, redness, and shortness of breath

- muscle and bone pain
- nausea
- decreased appetite
- urinary tract infection

The most common side effects of BAVENCIO when given with axitinib in people with RCC include:

- diarrhea
- feeling tired
- high blood pressure
- muscle and bone pain
- nausea
- mouth sores
- blisters or rash on the palms of your hands and soles of your feet

- hoarseness
- decreased appetite
- low levels of thyroid hormone
- rash
- liver problems
- cough
- shortness of breath
- stomach area (abdomen) pain
- headache

These are not all the possible side effects of BAVENCIO.
Call your doctor for medical advice about side effects. You may report side effects to FDA at 1-800-FDA-1088.

General information about the safe and effective use of BAVENCIO.
Medicines are sometimes prescribed for purposes other than those listed in a Medication Guide. You can ask your pharmacist or healthcare provider for information about BAVENCIO that is written for health professionals.

What are the ingredients in BAVENCIO?
Active ingredient: avelumab
Inactive ingredients: D-mannitol, glacial acetic acid, polysorbate 20, sodium hydroxide, and Water for Injection
Manufactured by: EMD Serono, Inc., Boston, MA 02210, USA, U.S. License No. 1773.
Marketed by: EMD Serono, Inc., MA, USA.
BAVENCIO is a trademark of Merck KGaA, Darmstadt, Germany.
For more information, call toll-free 1-844-826-8371 or go to www.bavencio.com.

This Medication Guide has been approved by the U.S. Food and Drug Administration.

Revised: 06/2025

PRINCIPAL DISPLAY PANEL - 10 mL Vial Carton

NDC 44087-3535-1

BAVENCIO®
(avelumab)
Injection

200 mg/10 mL
(20 mg/mL)

For intravenous infusion
after dilution
Single-dose vial
Discard unused portion.

Dispense the enclosed
Medication Guide to each
patient.

1 vial

Rx only

EMD
SERONO